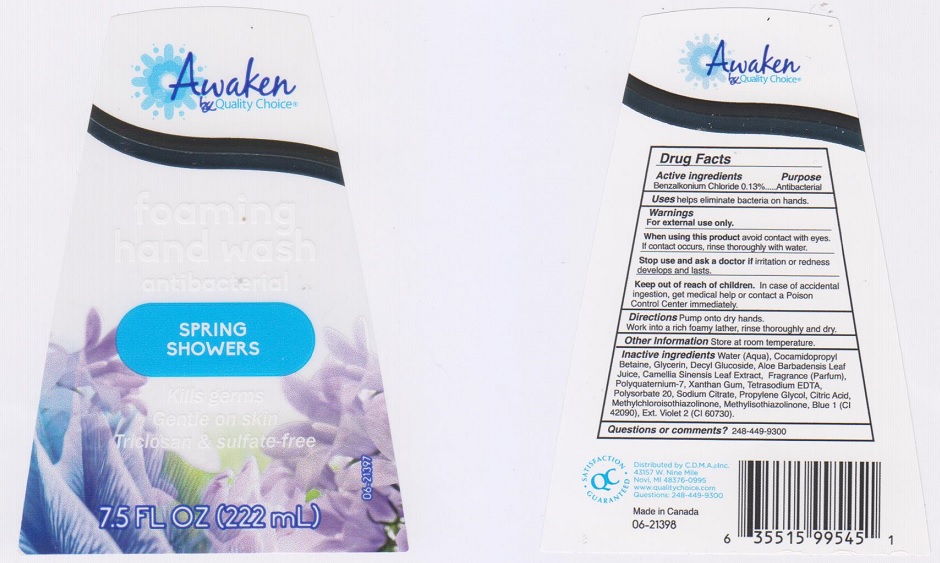 DRUG LABEL: Awaken by Quality Choice Foaming Hand Wash
NDC: 63868-115 | Form: SOAP
Manufacturer: Chain Drug MArketing Association Inc
Category: otc | Type: HUMAN OTC DRUG LABEL
Date: 20160822

ACTIVE INGREDIENTS: BENZALKONIUM CHLORIDE 1.3 mg/1 mL
INACTIVE INGREDIENTS: WATER; COCAMIDOPROPYL BETAINE; GLYCERIN; DECYL GLUCOSIDE; ALOE VERA LEAF; GREEN TEA LEAF; POLYQUATERNIUM-7 (70/30 ACRYLAMIDE/DADMAC; 1600000 MW); XANTHAN GUM; EDETATE SODIUM; POLYSORBATE 20; SODIUM CITRATE; PROPYLENE GLYCOL; CITRIC ACID MONOHYDRATE; METHYLCHLOROISOTHIAZOLINONE; METHYLISOTHIAZOLINONE; FD&C BLUE NO. 1; EXT. D&C VIOLET NO. 2

DRUG FACTS

Active ingredient

Benzalkonium Chloride 0.13%

Purpose

Antibacterial

Uses

helps eliminate bacterial on hands.

Warnings

For external use only.

When using this product

avoid contact with eyes. If contact occurs, rinse thoroughly with water.

Stop use and ask a doctor if

irritation or redness develops and lasts.

Keep out of reach of children.

In case of accidental ingestion, get medical help or contact a Poison Control Center immediately.

Directions

Pump onto dry hands. Work into a rich foamy lather, rinse thoroughly and dry.

Other information

Store at room temperature.

Inactive ingredients

Water (Aqua), Cocamidopropyl Betaine, Glycerin, Decyl Glucoside, Aloe Barbadensis Leaf Juice, Camellia Sinensis Leaf Extract, Fragrance (Parfum), Polyquaternium-7, Xanthan Gum, Tetrasodium EDTA, Polysorbate 20, Sodium Citrate, Propylene Glycol, Citric Acid, Methylchloroisothiazolinone, Methylisothiazolinone, Blue1 (CI 42090), Ext. Violet 2 (CI 60730).

Questions or comments?

1-248-449-9300